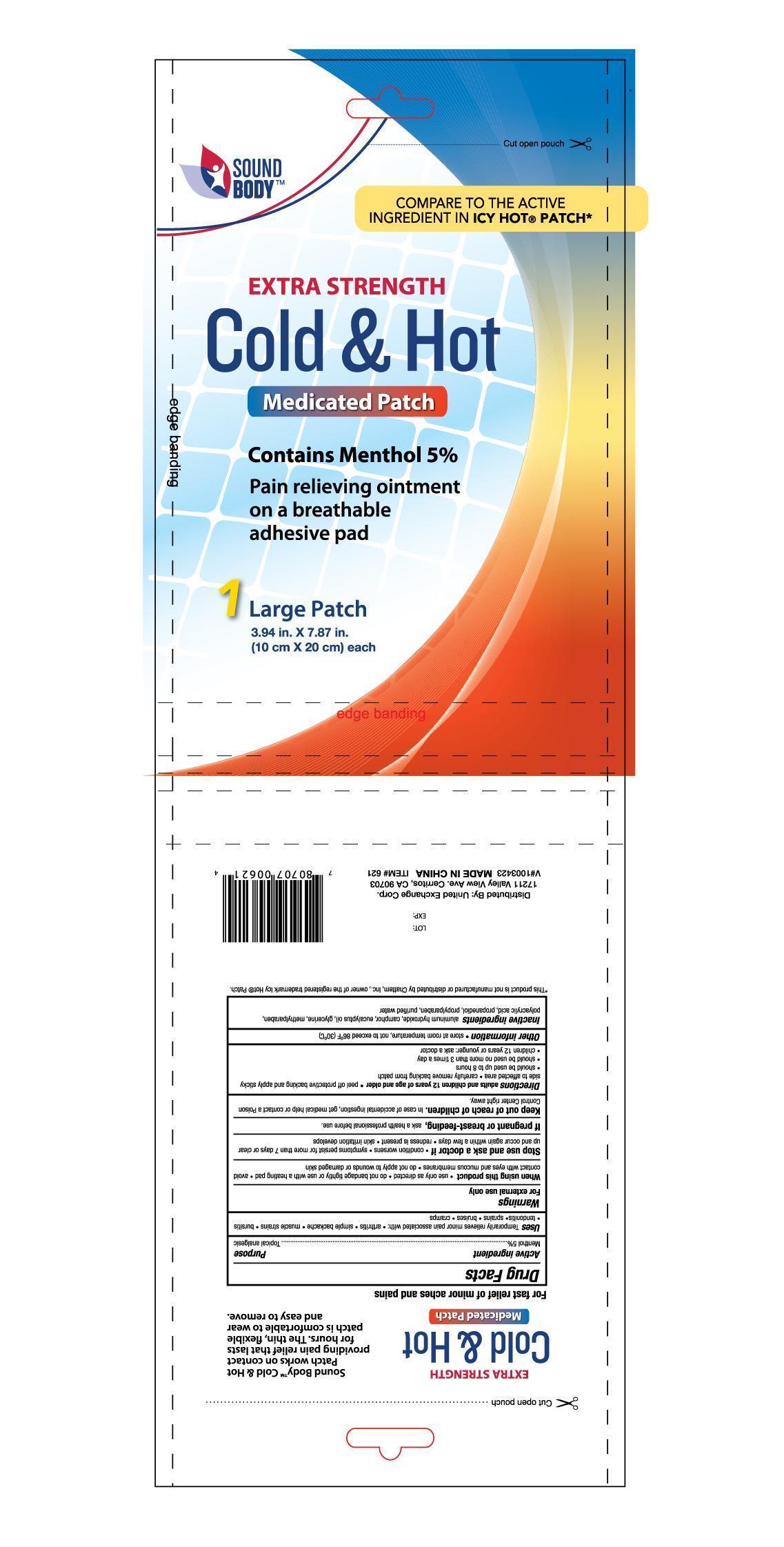 DRUG LABEL: Sound Body Extra Strength Cold and Hot Medicated
NDC: 65923-621 | Form: PATCH
Manufacturer: United Exchange Corp.
Category: otc | Type: HUMAN OTC DRUG LABEL
Date: 20150806

ACTIVE INGREDIENTS: MENTHOL 50 mg/1 g
INACTIVE INGREDIENTS: ALUMINUM HYDROXIDE; EUCALYPTUS OIL; GLYCERIN; METHYLPARABEN; PROPYLPARABEN; WATER

Active ingredeint Purpose

Menthol 5%.............................................................................. Topical analgesic

Uses

Temporarily relieves minor pain associated with:

- arthritis
- simple backache
- muscle strains
- bursitis
- tendonitis
- sprains
- bruises
- cramps

Warnings

For external use only

When using this product

- use only as directed
- do not bandage tightly or use with a heating pad
- avoid contact with eyes and mucous membranes
- redness is present
- skin irritation develops

Stop use and ask a doctor if

- condition worsens
- symptoms persist for more than 7 days or clear up and occur again within a few days
- redness is present
- skin irritation develops

PREGNANCY OR BREAST FEEDING

If pregnant or breast-feeding, ask a health professional before use

Keep out of reach of children. In case of accidental ingestion, get medical help or contact a Poison Control Center right away

Directions

adults and children 12 years of age and older

- peel off protective backing and apply sticky side to affected area
- carefully remove backing from patch
- should be used up to 8 hours
- should be used no more than 3 times a day
- children 12 years of younger: ask a doctor

Other information

- store at room temperature, not to exceed 86°F (30°C)

Inactive ingredients

aluminum hydroxide, camphor, eucalyptus oil, glycerine, methylparaben, polyacrylic acid, propaneidol, propylparaben, purified water

DOSAGE AND ADMINISTRATION

DISTRIBUTED BY:

UNITED EXCHANGE CORP.

17211 VALLEY VIEW AVE.

CERRITOS, CA 90703

MADE IN CHINA